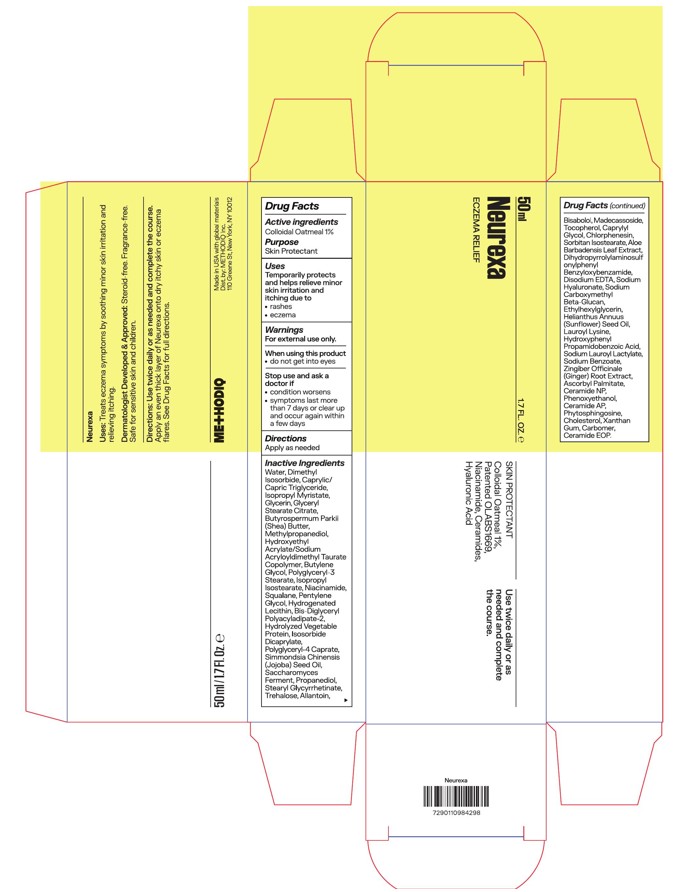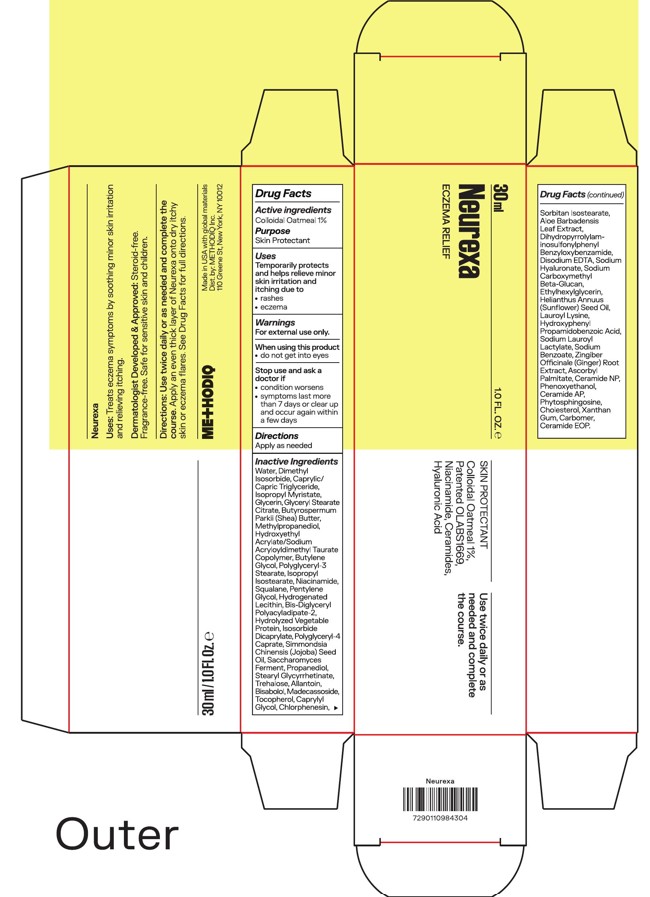 DRUG LABEL: Neurexa
NDC: 87110-004 | Form: CREAM
Manufacturer: METHODIQ INC.
Category: otc | Type: HUMAN OTC DRUG LABEL
Date: 20260203

ACTIVE INGREDIENTS: OATMEAL 10 mg/1 mL
INACTIVE INGREDIENTS: TREHALOSE; PENTYLENE GLYCOL; STEARYL GLYCYRRHETINATE; BISABOLOL; SODIUM BENZOATE; GINGER; HELIANTHUS ANNUUS (SUNFLOWER) SEED OIL; BUTYROSPERMUM PARKII (SHEA) BUTTER; BUTYLENE GLYCOL; POLYGLYCERYL-4 CAPRATE; ISOPROPYL ISOSTEARATE; SIMMONDSIA CHINENSIS (JOJOBA) SEED OIL; TOCOPHEROL; PHYTOSPHINGOSINE; METHYLPROPANEDIOL; EDETATE DISODIUM; XANTHAN GUM; HYDROGENATED SOYBEAN LECITHIN; SODIUM HYALURONATE; HYDROXYPHENYL PROPAMIDOBENZOIC ACID; ISOSORBIDE DICAPRYLATE; CERAMIDE NP; PHENOXYETHANOL; CERAMIDE AP; WATER; ISOPROPYL MYRISTATE; GLYCERIN; CHOLESTEROL; CERAMIDE 1; SODIUM LAUROYL LACTYLATE; BIS-DIGLYCERYL POLYACYLADIPATE-2; PROPANEDIOL; DIMETHYL ISOSORBIDE; LAUROYL LYSINE; ASCORBYL PALMITATE; CARBOMER; MADECASSOSIDE; ALOE BARBADENSIS LEAF; SODIUM CARBOXYMETHYL .BETA.-GLUCAN (DS 0.65-0.85); ETHYLHEXYLGLYCERIN; CHLORPHENESIN; CAPRYLYL GLYCOL; ALLANTOIN; HYDROXYETHYL ACRYLATE/SODIUM ACRYLOYLDIMETHYL TAURATE COPOLYMER (45000 MPA.S AT 1%); CAPRYLIC/CAPRIC TRIGLYCERIDE; NIACINAMIDE; SQUALANE; GLYCERYL STEARATE CITRATE; POLYGLYCERYL-3 STEARATE; SORBITAN ISOSTEARATE

Neurexa

Active ingredient

Colloidal Oatmeal 1%

Purpose

Active ingredients: Colloidal Oatmeal 1%

Purpose: Skin Protectant

Uses

Temporarily protects and helps relieve minor skin irritation and itching due to:

• rashes

• eczema

Warnings

For external use only.

When using this product

• do not get into eyes

Stop use and ask a doctor if

• condition worsens

• symptoms last more than 7 days or clear up and occur again within a few days

Keep out of reach of children. If swallowed, get medical help or contact a Poison Control Center right away.

Directions

Apply as needed

Inactive ingredients

Water, Dimethyl

Isosorbide, Caprylic/

Capric Triglyceride,

Isopropyl Myristate,

Glycerin, Glyceryl Stearate

Citrate, Butyrospermum

Parkii (Shea) Butter,

Methylpropanediol,

Hydroxyethyl

Acrylate/Sodium

Acryloyldimethyl Taurate

Copolymer, Butylene

Glycol, Polyglyceryl-3

Stearate, Isopropyl

Isostearate, Niacinamide,

Squalane, Pentylene

Glycol, Hydrogenated

Lecithin, Bis-Diglyceryl

Polyacyladipate-2,

Hydrolyzed Vegetable

Protein, Isosorbide

Dicaprylate, Polyglyceryl-4

Caprate, Simmondsia

Chinensis (Jojoba) Seed

Oil, Saccharomyces

Ferment, Propanediol,

Stearyl Glycyrrhetinate,

Trehalose, Allantoin,

Bisabolol, Madecassoside,

Tocopherol, Caprylyl

Glycol, Chlorphenesin,

Sorbitan Isostearate,
Aloe Barbadensis Leaf Extract,
Dihydroxypropylamino Isobutyphenyl Benzylbenzamide,
Disodium EDTA,
Sodium Hyaluronate,
Sodium Carboxymethyl Beta-Glucan,
Ethylhexylglycerin,
Helianthus Annuus (Sunflower) Seed Oil,
Lauroyl Lysine,
Hydroxyphenyl Propamidobenzoic Acid,
Sodium Lauroyl Lactylate,
Sodium Benzoate,
Zingiber Officinale (Ginger) Root Extract,
Ascorbyl Palmitate,
Ceramide NP,
Phenoxyethanol,
Ceramide AP,
Phytosphingosine,
Cholesterol,
Xanthan Gum,
Carbomer,
Ceramide EOP.

PACKAGE LABEL

30ml 1.0 Fl. Oz.

Neurexa

Eczema Relief